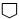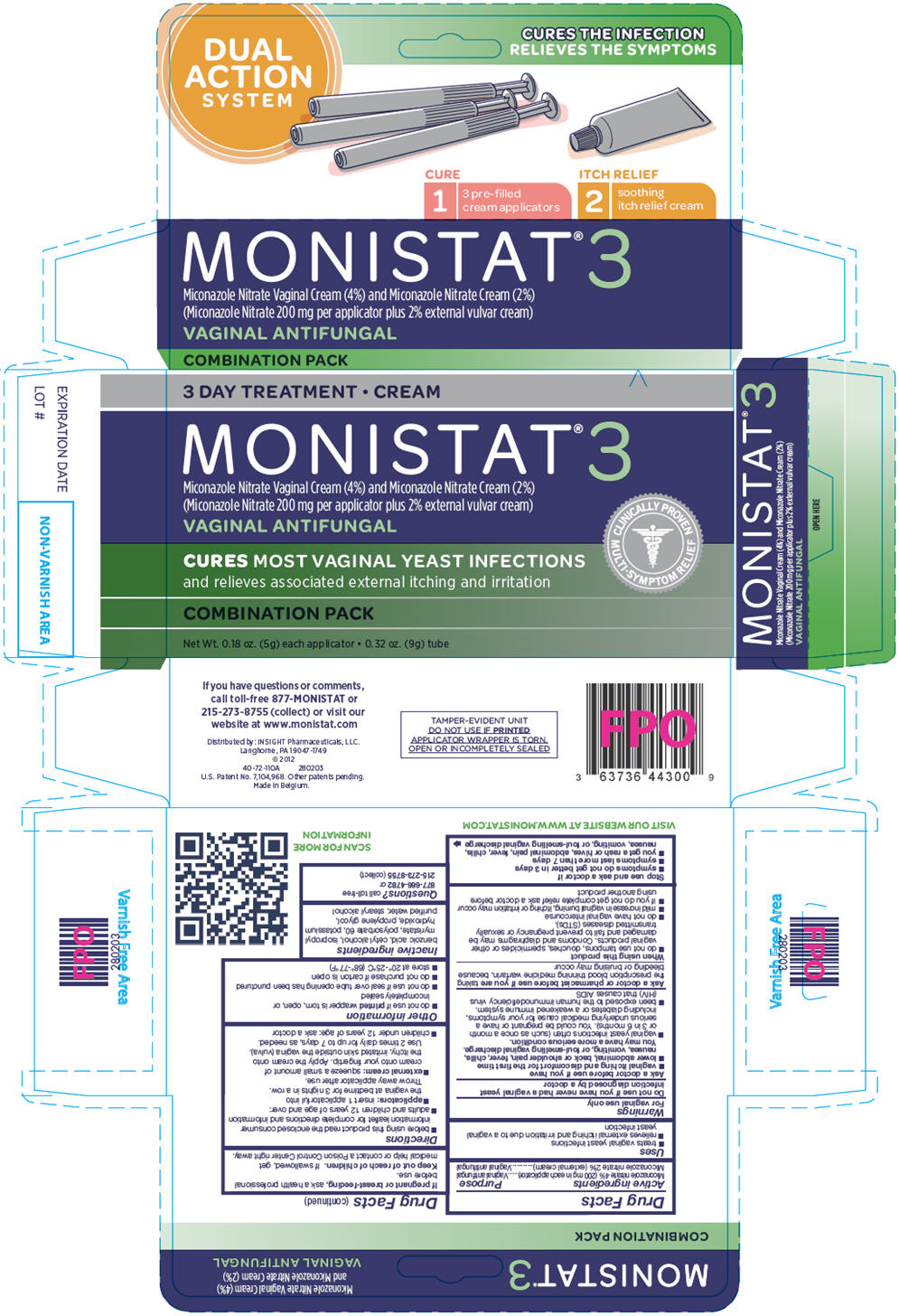 DRUG LABEL: Monistat 3 Combination Pack
NDC: 63736-018 | Form: KIT | Route: VAGINAL
Manufacturer: Insight Pharmaceuticals
Category: otc | Type: HUMAN OTC DRUG LABEL
Date: 20120802

ACTIVE INGREDIENTS: Miconazole Nitrate 200 mg/1 1; Miconazole Nitrate 10 mg/0.5 g
INACTIVE INGREDIENTS: HYDROGENATED COCONUT OIL; HYDROGENATED PALM KERNEL OIL; Benzoic Acid; Cetyl Alcohol; Isopropyl Myristate; Polysorbate 60; Potassium Hydroxide; Propylene glycol; Water; Stearyl Alcohol

MONISTAT® 3
COMBINATION PACK

Miconazole Nitrate Vaginal Suppositories (200 mg) and Miconazole Nitrate Vaginal Cream
(2%)
Vaginal Antifungal

DRUG FACTS

ACTIVE INGREDIENT

Active ingredients | Purpose
Miconazole nitrate (200 mg in each suppository) | Vaginal antifungal
Miconazole nitrate 2% (external cream) | Vaginal antifungal

Uses

- treats vaginal yeast infections
- relieves external itching and irritation due to a vaginal yeast infection

Warnings

For vaginal use only

Do not use if you have never had a vaginal yeast infection diagnosed by a doctor

Ask a doctor before use if you have

- vaginal itching and discomfort for the first time
- lower abdominal, back or shoulder pain, fever, chills, nausea, vomiting, or foul-smelling vaginal discharge. You may have a more serious condition.
- vaginal yeast infections often (such as once a month or 3 in 6 months). You could be pregnant or have a serious underlying medical cause for your symptoms, including diabetes or a weakened immune system.
- been exposed to the human immunodeficiency virus (HIV) that causes AIDS

Ask a doctor or pharmacist before use if you are taking the prescription blood thinning medicine warfarin, because bleeding or bruising may occur

When using this product

- do not use tampons, douches, spermicides or other vaginal products. Condoms and diaphragms may be damaged and fail to prevent pregnancy or sexually transmitted diseases (STDs).
- do not have vaginal intercourse
- mild increase in vaginal burning, itching or irritation may occur
- if you do not get complete relief ask a doctor before using another product.

Stop use and ask a doctor if

- symptoms do not get better in 3 days
- symptoms last more than 7 days
- you get a rash or hives, abdominal pain, fever, chills, nausea, vomiting, or foul-smelling vaginal discharge

PREGNANCY OR BREAST FEEDING

If pregnant or breast-feeding, ask a health professional before use.

Keep out of reach of children. If swallowed, get medical help or contact a Poison Control Center right away.

Directions

- before using this product read the enclosed consumer information leaflet for complete directions and information
- adults and children 12 years of age and over:
- suppositories: insert 1 suppository into the vagina at bedtime for 3 nights in a row. Throw away applicator after use.
- external cream: squeeze a small amount of cream onto your fingertip. Apply the cream onto the itchy, irritated skin outside the vagina. Use 2 times daily for up to 7 days, as needed.
- children under 12 years of age: ask a doctor

Other information

- do not use if printed suppository blister is torn, open or incompletely sealed
- do not use if seal over tube opening has been punctured or embossed design is not visible
- do not purchase if carton is open
- store at 20°-25°C (68°-77°F)

Inactive ingredients

suppository: hydrogenated vegetable oil base

external cream: benzoic acid, cetyl alcohol, isopropyl myristate, polysorbate 60, potassium hydroxide, propylene glycol, purified water, stearyl alcohol

QUESTIONS

Questions? If you have any questions or comments, please call 1-877-666-4782
Visit our website @ www.monistat.com

PACKAGE LABEL

PRINCIPAL DISPLAY PANEL - Kit Carton

3 DAY TREATMENT • CREAM

MONISTAT® 3
Miconazole Nitrate Vaginal Cream (4%) and Miconazole Nitrate Cream (2%)
(Miconazole Nitrate 200 mg per applicator plus 2% external vulvar cream)
VAGINAL ANTIFUNGAL

CLINICALLY PROVEN
MULTI-SYMPTOM RELIEF

CURES MOST VAGINAL YEAST INFECTIONS
and relieves associated external itching and irritation

COMBINATION PACK

Net Wt. 0.18 oz. (5g) each applicator • 0.32 oz. (9g) tube